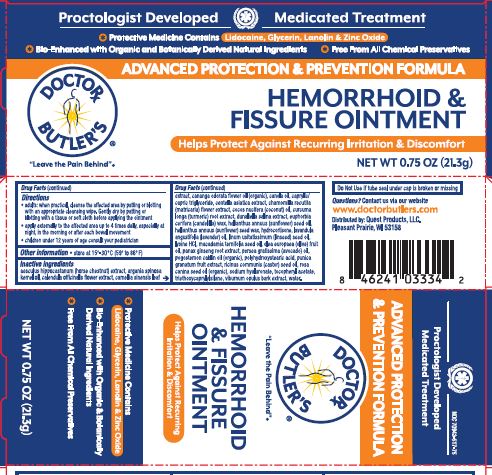 DRUG LABEL: Doctor Butler Hemorrhoid and Fissure
NDC: 70942-517 | Form: OINTMENT
Manufacturer: Beyond Health, PA
Category: otc | Type: HUMAN OTC DRUG LABEL
Date: 20250723

ACTIVE INGREDIENTS: GLYCERIN 37.5 g/100 g; LIDOCAINE 4 g/100 g; LANOLIN 12.5 g/100 g; ZINC OXIDE 5 g/100 g
INACTIVE INGREDIENTS: GREEN TEA LEAF; TRIETHOXYCAPRYLYLSILANE; HYALURONATE SODIUM; VIBURNUM OPULUS WHOLE; WATER; ASIAN GINSENG; AVOCADO OIL; POMEGRANATE; CANDELILLA WAX; MEDIUM-CHAIN TRIGLYCERIDES; HYDROCORTISONE; CASTOR OIL; ROSA CANINA SEED OIL; MACADAMIA OIL; OLIVE OIL; POLYHYDROXYSTEARIC ACID (2300 MW); POGOSTEMON CABLIN LEAF OIL; CENTELLA ASIATICA TRITERPENOIDS; SUNFLOWER OIL; LAVENDER OIL; LYSINE HYDROCHLORIDE; LINSEED OIL; COCONUT OIL; CHAMOMILE; CANOLA OIL; CANANGA OIL; HORSE CHESTNUT; TURMERIC; ARGAN OIL; DUNALIELLA SALINA; HELIANTHUS ANNUUS (SUNFLOWER) SEED WAX; CALENDULA OFFICINALIS FLOWER; .ALPHA.-TOCOPHEROL ACETATE

Doctor Butler Advanced Formula Ointment

Active ingredients

Glycerin 37.5%

Lanolin 12.5%

Lidocaine 4.0%

Zinc Oxide 5.0%

Purpose

Protectant

Protectant

Analgesic (pain relief)

Astringent

Uses

- helps relieve the local or anorectal itching and discomfort associated with hemorrhoids

Warnings

For external use only inclluding the skin of the anal canal

When using this product

- do not exceed the recommended daily dosage unless directed by a doctor
- do not put this product into the rectum by using fingers or any mechanical device or applicator

Stop use and ask a doctor if

- condition worsens or does not improve within seven (7) days
- bleeding occurs
- an allergic reaction develops
- the symptom being treated does not subside or if redness, irritation, swelling, pain or other symptoms develop or increase

If pregnant or breast-feeding

ask a health care professional before use.

Keep out of reach of children

If swallowed, seek medical help or contact a Poison Control Center right away.

Directions

- adults; when practical, cleanse the affected area by patting or blotting with an appropriate cleansing wipe. Gently dry by patting or blotting with a tissue or soft cloth before appying the ointment
- apply externally to the affected area up to 4 times daily, especially at night, in the morning or after each bowel movement
- children under 12 years of age consult your pediatrician

Other information

- store at 15º-30º C (59º-86º F)

Inactive ingredients

Aesculus Hippocastanum (Horse Chestnut) Extract

Argania Spinosa Kernel Oil

Calendula Officinalis Flower Extract

Camellia Sinensis Leaf Extract

Cananga Odorata Flower Oil (organic)

Canola Oil

Caprylic/Capric Triglyceride

Centella Asiatica Extract

Chamomilla Recutita (Matricaria) Flower Extract

Cocos Nucifera (Coconut) Oil

Curcuma Longa (Turmeric) Root Extract

Dunaliella Salina Extract

Euphorbia Cerifera (Candelilla) Wax

Helianthus Annuus (Sunflower) Seed Oil

Helianthus Annuus (Sunflower) Seed Wax

Hydrocortisone

Lavandula Angustifolia (Lavender) Oil

Linum Usitatissimum (Linseed) Seed Oil

Lysine HCl

Macadamia Ternifolia Seed Oil

Olea Europaea (Olive) Fruit Oil

Panax Ginseng Root Extract

Persea Gratissima (Avocado) Oil

Pogostemon Cablin Oil (organic)

Polyhydroxystearic Acid

Punica Granatum Fruit Extract

Ricinus Communis (Castor) Seed Oil

Rosa Canina Seed Oil (organic)

Sodium Hyaluronate

Tocopheryl Acetate

Triethoxycaprylylsilane

Viburnum Opulus Bark Extract

Water